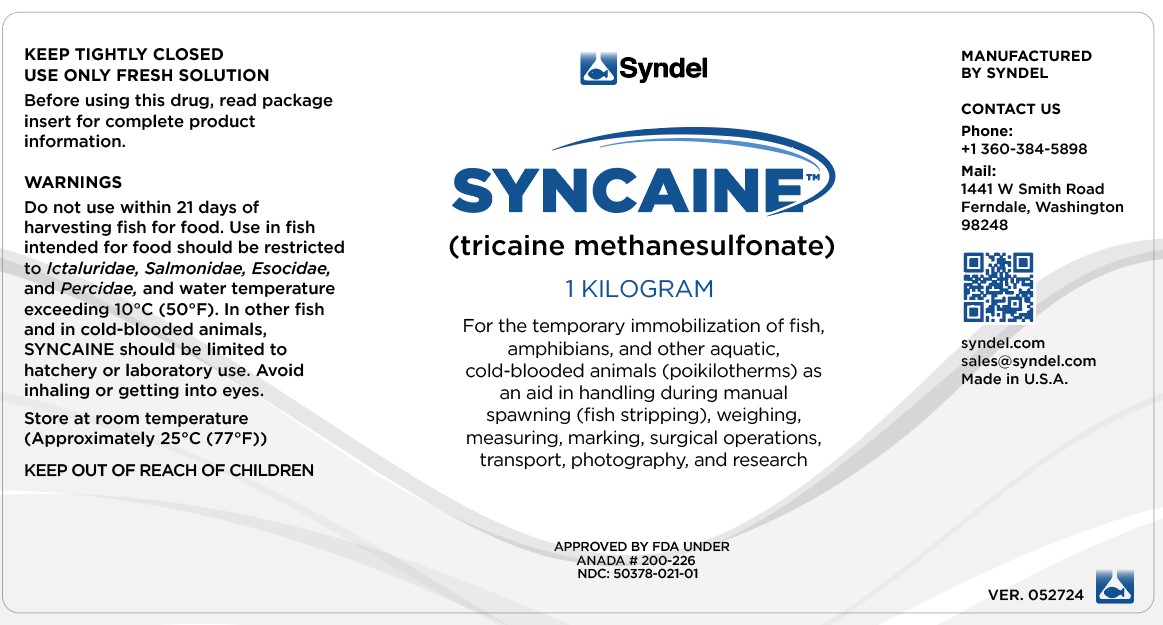 DRUG LABEL: SYNCAINE
NDC: 50378-021 | Form: POWDER, FOR SOLUTION
Manufacturer: Western Chemical Inc.
Category: animal | Type: OTC ANIMAL DRUG LABEL
Date: 20250530

ACTIVE INGREDIENTS: TRICAINE METHANESULFONATE 1000 mg/1 g

SYNCAINE
(tricaine methanesulfonate)

DESCRIPTION

SYNCAINE
(tricaine methanesulfonate)

KEEP TIGHTLY CLOSED USE ONLY FRESH SOLUTION

Before using this drug, read package insert for complete
product information.

Store at room temperature (Approximately 25°C (77°F))

KEEP OUT OF THE REACH OF CHILDREN

SYNCAINE is intended for the temporary immobilization of fish, amphibians, and other aquatic, cold-blooded animals (poikilotherms) as an aid in handling during manual spawning (fish stripping), weighing, measuring, marking, surgical operations, transport, photography, and research.

Warnings

Do not use within 21 days of harvesting fish for food. Use in fish intended for food should be restricted to Ictaluridae, Salmonidae, Esocidae, and Percidae, and water temperature exceeding 10ºC (50ºF). In other fish and in cold-blooded animals, SYNCAINE should be limited to hatchery or laboratory use. Avoid inhaling or getting into eyes.

Chemistry

SYNCAINE is the methanesulfonate of meta-amino benzoic acid ethylester, or simply ethyl m-amino benzoate. It is thus an isomer of benzocaine having the formula C9H11O2N + CH3SO3H

SYNCAINE is a fine white crystalline powder. Its molecular weight is 261.3. Soluble to 11%, it forms clear, colorless acid solutions in water.

Toxicology

Comparative toxicologic studies carried out on fish and frogs gave the following results:
FISH TOXCITY STUDIES - The toxicity of SYNCAINE was measured by standard methods in laboratory bioassays with rainbow trout, brown trout, brook trout, lake trout, northern pike, channel catfish, bluegill, largemoth bass and walleye. The 24, 48 and 96 hour LC50 (lethal concentration for 50 percent of the animals) values for trout ranged from 52 to 31 mg/liter; for northern pike, from 56 to 48 mg/liter; for catfish, from 66 to 50 mg/liter; for bluegill and largemouth bass, from 61 to 39 mg/liter; and for walleye, the values were 49 to 46 mg/liter.
Safety Index:The safety indices for SYNCAINE refer to the margin between concentrations which cause anesthesia and mortality. They are expressed by the quotient of the lethal concentration for 50 percent of the fish (LC50) and the effective concentration for 50 percent of the fish (EC50)

Safety Indices for Rainbow Trout and Channel Catfish at 12°C (54°F)

Species | Exposure (min.) | LC50 (mg/liter) | EC50 (mg/liter) | Index
Rainbow Trout^1 " " Channel Catfish^2 " " | 15 30 60 15 30 60 | 65 57 56 139 118 110 | 32 32 29 47 45 46 | 2.0 1.8 1.9 3.0 2.6 2.4

FROG TOXICITY STUDIES3 - Frogs were put into various concentrations of SYNCAINE for 30 minutes and then transferred to tap water in order to determine LC50. The LC50 was 6.2 percent SYNCAINE. Therefore, the anesthetic must be used in very high concentration before it is fatal to frogs.

I. DIRECTIONS FOR USE ON FISH

CONCENTRATIONS SYNCAINE is effective and safe for the anesthesia of fish when used as directed. Its use is governed by, and can be tailored to, the needs of individual fishery personnel. Sedation and various rates of anesthetization are controlled by the concentration. The versatility of SYNCAINE is demonstrated by the fact that it has been used in fisheries at levels ranging from 10 to 1,000 mg/liter^3. The action of the anesthetic is slowed at cooler temperatures, in extremely soft water (approximately 10 mg/liter of CaCO3, or less), and in larger fish^4. Also, efficacy may vary with species^4.Thus, it is imperative that preliminary tests of anesthetic to determines the desired rates of anesthesia and exposure times for the specific lots of fish under prevailing conditions.

The following tables may be used as guidelines in selecting concentrations of SYNCAINE for the anesthetization of various fishes:

Table 1: Concentration Required for Rapid Anesthesia
(Induction time less than 2-5 minutes; used in spawning, marking, measuring, and some surgical operations)

Fish | Temperature | Concentration (mg/liter) | Max. tolerated exposure time* (min.) | Recovery time in fresh water (min.)
Salmonidae^4 (Pacific and Atlantic salmon; trout; chars; etc.) | 7 - 17°C (45 - 63°F) | 80 - 135 | 4 - 12 | 3 - 19
Escoidae^5 (Norther pike; muskellunge) | 8 - 12°C (46 - 54°F) | 150 | 8 - 28 | 8 - 31
Cyprindae^3 (Carp; goldfish) | 16°C (61°F) | 150 - 200
Ictaluridae^2 (Channel catfish) | 7 - 27°C (45 - 81°F) | 140 - 270 | 4 - 11 | 3 - 24
Centrarchidae^4 (Bluegill; largemouth bass) | 10 - 27°C (50 - 81°F) | 260 - 330 | 3 - 5 | 7 - 11
Percidae ^3 (Walleye) | 10 - 16°C (50 - 61°F) | 100 - 120 | 7 - 18 | 5 - 40
Pet and Tropical^1 Live-bearers Egg layers | 24 - 27°C (75 - 81°F) 24 - 27°C (75 - 81°F) | 85 75 | 12 hrs 12 hrs

* Maximum tolerated exposure (in minutes) of fish to SYNCAINE solution.

Table 2: Concentration Required for Moderately Rapid Anesthesia
(Induction time less than 15-20 minutes; used in surgical operations and in spawning and marking where longer exposures are more important than rapid immobilization)

Fish | Temperature | Concentration (mg/liter | Maximum tolerated exposure time* (min.) | Recovery time in fresh water (min.)
Salmonidae^4 (Pacific and Atlantic salmon; trout; chars; etc.) | 7 - 17°C (45 - 63°F) | 50 - 60 | 30 or > | 2 - 20
Ictaluridae^2 (Channel catfish) | 7 - 27°C (45 - 81°F) | 70 | 30 or > | 1 - 10

*Maximum tolerated exposure time (in minutes) of fish to SYNCAINE solution.

Table 3: Concentrations Required for Sedation
(Induction within 15 minutes; used in fish transport)

Fish | Temperature | Concentration (mg/liter) | Maintanance of Sedation (hr.)
Salmonidae^4 (Pacific and Atlantic salmon; trout; chars; etc.) | 7 - 17°C (45 - 83°F) | 15 - 30 | 6
Escoidae^5 (Chain Pickeral) |  | 40
Ictaluridae^2 (Channel catfish) | 7 - 27°C (45 - 81°F) | 20 - 40 | 6
Centrarchidae^2 (Bluegills) |  | 25 | 8 - 13
Pet and Tropical^1 [Bettas, Pirhanas, etc. (uncrowded)] Goldfish | 24 - 27°C (75 - 81°F) 24 - 27°C (75 - 81°F) | 66 37 | 48 48

IMPORTANT: Since, in many cases, relatively rapid rates of anesthesia can be achieved only by exceeding the lethal concentration of SYNCAINE, it is necessary to return anesthetized fish to fresh water before they are overexposed. Excessive exposures are avoided by observing the following sensory and motor responses of the fish which characterize progressively deeper levels of anesthesia.
Sedation - Decreased reactivity to visual and vibrational stimuli; opercular activity reduced.
Total loss of equilibrium - Fish turns over; locomotion increases; fish swims or extends fins in response to pressure on caudal fin or peduncle.
Total loss of reflex - No response to pressure on caudal fin or peduncle; opercular rate slow and erratic.
Medullary collapse - Opercular activity ceases.

Laboratory and field investigations^3,9, have shown that the action of SYNCAINE is readily reversed when the fish are transferred to fresh water before opercular activity ceases. Additional exposure following medullary collapse may result in mortality. A rough estimate of the safe total exposure can be made by multiplying the time required for anesthesia by a factor of 2 or 3.

WATER
Since SYNCAINE is very soluble (1:9) in water, it dissolves with equal readiness in spring water, tap water, or seawater. Do not use distilled or deionized water, or water containing chlorine, heavy metals (copper, zinc, etc.), or other toxic contaminants. The anesthetic solution should be well oxygenated, and its temperature should be similar to that of the water from which fish are taken. In the field, many water quality problems are eliminated by using natural water to which the fish are acclimated, provided the water does not possess high chemical or biologic oxygen demand.

METHODS OF APPLICATION
1. General anesthesia: - For most situations where rapid or moderately rapid anesthesia is required, SYNCAINE may be applied in a bath, i.e., the fish are immersed in the anesthetic solution. Containers may be of glass, plastic, steel, aluminum, or other suitable material. However, do not use galvanized or brass containers unless treated or sealed to prevent dissolution of zinc. Size of container is determined by individual needs, but the fish should not be overcrowded. Discard anesthetic solutions when a loss in potency is noted, or when the solutions become fouled with mucus or excrement.
2. For surgery and certain physiologic studies, the fish may be anesthetized to loss of reflex, removed from the anesthetic, and then positioned so that the gills are bathed in a sedating concentration of SYNCAINE. Some investigators have developed flowing, recirculating systems for bathing the gills with anesthetic during surgery.

Large fishes such as sharks and rays are anesthetized within minutes by spraying the gills with a 1g/liter solution of SYNCAINE^10 . The application is made by means of a water pistol, bulb syringe, hand pump, etc.

3. Transport - SYNCAINE has been used to sedate fish during transport. It is more successful in cold than in warm water, and it is instrumental in reducing injuries because of hyperactivity. Fish are usually transported by means of distribution units (tank trucks), or by air in plastic bags^11,12. In either case, the fish should be fasted before-hand to reduce metabolic wastes. Also, some workers suggest pre-transport sedation for several hours to lower metabolism. With distribution units, the fish may be fasted and sedated prior to loading. The anesthetic solution is prepared in the distribution unit and oxygenated. Then, the fish are added and temperature acclimated. In air shipments, the anesthetic solution is placed in a suitable plastic bag, the sedated fish are added, the bag inflated with oxygen, tied securely, and placed in a second bag. This bag is also tied, and then placed on ice in an insulated container^13. A modification of this method involves complete anesthesia of the fish, and placing them in water bags which contain no anesthetic. In any case, upon arrival, the fish should be acclimated slowly to new environmental temperatures.

PREPARATION OF SYNCAINE SOLUTIONS
Prior to use, SYNCAINE may be weighed out into amounts which are convenient for the volume of water to be used. A handy unit is 2 g. since this quantity in 5 gallons of water yields a concentration of about 100 mg/liter. For rough approximations, one level teaspoonful contains 2.0 to 2.5 g. Thus a level teaspoonful of anesthetic in 5 gallons gives a concentration of about 120 mg/liter.

To convert mg/liter into g/gal.: multiply number of mg. by 0.00378
e.g. 80 mg/liter = 80 x 0.00378 = 0.302 g./gal.
To convert mg/liter into a ratio of SYNCAINE to water: divide 1,000,000 by the number of mg.
e.g. 80 mg/liter = 1,000,000 / 80 = 1:12,500

LIMITATIONS IN USE
Since SYNCAINE is taken up into the blood of fish, residues of the drug may occur in edible tissues. However, the residues dissipate rapidly after the fish are placed in fresh water^14. Thus, treated fish which may be used for food must be held in fresh water above 10°C. (50°F.) for a period of 21 days.

Withdrawal in fresh water is unnecessary for non food fishes such as goldfish, bait fish, and ornamentals. Also, withdrawal is unnecessary for sublegal sizes of the following species of fish because they are not used as food immediately following anesthesia (Table 4).

Table 4 - Sublegal Sizes of Fish Species not used as Food Immediately after Anesthesia^15

Species | Size (in.) | Species | Size (in.)
Pink salmon | 6 | Lake trout | 5
Chum salmon | 6 | Splake trout | 6
Coho salmon | 6 | Grayling | 6
Sockeye salmon | 6 | Norther pike | 12
Chinook salmon | 6 | Muskellunge | 12
Cutthroat trout | 6 | Channel catfish | 6
Steelhead trout | 8 | Flathead catfish | 6
Rainbow trout | 6 | Bluegill | 3
Atlantic dalmon | 10 | Redear sunfish | 3
Brown trout | 6 | Smallmouth bass | 5
Brook trout | 6 | Largemouth bass | 5
 |  | Walleye | 6

PRECAUTIONS

1. Avoid inhaling SYNCAINE or getting it into the eyes.
2. Always conduct preliminary tests with SYNCAINE to determine desired rates of anesthesia and optimal length of exposure.
3. Do not overexpose fish to lethal levels of SYNCAINE.
4. Do not anesthetize more fish than can be handled effectively.
5. Do not contaminate eggs or sperm with SYNCAINE when stripping fish.
6. Do not use water containing chlorine, or other toxic agents.
7. Ensure adequate oxygen in anesthetic solution.
8. Discard anesthetic solutions when fouled with mucus or metabolic wastes.
9. Do not discard SYNCAINE solutions into water supplies or natural waters.
10. Store SYNCAINE solutions in a cool place away from light.*
11. Discard stock solutions of SYNCAINE after several days.*
12. Treated fish destined for food must be held in fresh water above 10°C (50°F) for 21 days before use.

* The color of SYNCAINE solutions may change rapidly to yellow or brown when exposed to light. This does not affect activity in any significant way. However, for best results, use freshly prepared solutions. A 10 percent solution stored at room temperature shows no significant loss of potency after three days, but after 10 days, a brownish color and an activity decrease of 5 percent is observed.

II. GUIDELINES FOR USE ON AMPHIBIANS

Table 5. Effects of Varying Concentrations of SYNCAINE on Salamanders

Salamander | Concentration* | Duration of Anesthesia* | Remarks
EMBRYOS Ambystoma opacum LARVAE Ambystoma opacum ADULTS Newts Triturus sp. Triturus uridescens Mole salamanders Ambystoma opacum Ambystoma Tigrinum Ambystoma punctatum Mud-puppy Necturus maculosus | 1:10,1000 (3b) 1:3,000 (3c) 1:10,000 (3b) 1:12,000 (3f) 1:20,000 (3f) 1:3,000 (3c) 1:1,000 (3b) 1:3,000 (3b) 1:1,000 (3b) 1:10,000 (3b) 1:1,000 (3k) 1:3,000 (3g) 1:3,000 (3c) 1:2,000 (3j) 1:2,000 (3j) 1:1,500 (3i) | 2 days to 30 min. 2 days 10 - 15 min. 10 - 15 min. to 30 min. few min. 3 days few min. 2 days 20 min. 1 hour to 30 min. 15 - 30 min. 15 - 30 min. to 6 hours | No adverse effects No adverse effects No adverse effects No adverse effects No adverse effects No adverse effects No adverse effects No adverse effects No adverse effects No adverse effects ** ** Maintenance dose, 0.1 of induction concentration. At exposure to induction concentration for more than 20 - 30 minutes, renal circulation becomes sluggish or stops

* When an individual of any of the species listed is exposed at the designated concentration, the data available suggest that the animal may be safely maintained under anesthesia for the time noted. Prolonging exposure to the anesthetic beyond the time indicated may cause deaths. See PRECAUTIONS.

** Maintenance dose, 0.1 of induction concentration. At exposure to induction concentration for more than 20-30 minutes, renal circulation becomes sluggish or stops.

Table 6 - Effects of Varying Concentrations of SYNCAINE on Frogs

Frog | Concentration* | Duration of Anesthesia | Remarks
EMBRYOS TADPOLES Rana sp. Rana pipiens ADULTS Leopard frog Rana pipiens Eastern wood frog Rana sylvatica | 1:1,000 (3b) 1:10,000 (3b) 1:15,000 (3h) 1:1,000 (3j) 1:3,000 (3f) 1:10,000 (3b) 1:15,000 (3h) 1:5,000 (3k) 1:1,000 (3j) 1:3,333 (3a) variable (3c) 1:1,000 (3e) 1:3,000 (3c) 1:8,000 (3l) | few min. 2 days 3 days 30 min. 10 - 15 min. 2 days 3 days 5 hours 15 - 30 min. 2 min. 1 hour 30 min. to 30 min. 5 - 10 min. | No adverse effects No adverse effects No adverse effects No adverse effects No adverse effects only slightly under anesthesia

* When an individual of any of the species listed is exposed at the designated concentration, the data available suggest that the animal may be safely maintained under anesthesia for the time noted. Prolonging exposure to the anesthetic beyond the time indicated may cause deaths. See PRECAUTIONS.

AVAILABILITY OF SYNCAINE
Bottles of 1 kilogram, 100 grams, and 10 grams.

REFERENCES
1. Marking, L.L.: Investigations in Fish Control. 12. Toxicity of MS-222 to Selected
Fishes, U.S. Bureau of Sport Fisheries and Wildlife, Resource Publication 18, 1966.
2. Schoettger, R.A., Walker, C.R., Marking, L.L., and Julin, A.M.: MS-222 as an Anesthetic for Channel Catfish; its Toxicity, Efficacy, and Muscle Residues, U.S. Bureau of Sport
Fisheries and Wildlife, Resource Publication 33, 1967.
3. Personal communications:
a. Bernheimer, W.M., New York University College of Medicine, New York, N.Y. b. Butler, E.G., Princeton University, Dept. of Biology, Princeton, N.J.
c. Dalton, H.D., and Charipper, H.A., Washington Square College, Dept. of Biology
New York, N.Y.
d. Etkin, W., City College, Dept. of Biology, New York, N.Y. e. Goss, R.J., Brown University, Providence, R.I.
f. Kollros, J.J., State University, Iowa City, Iowa.
g. Manner, H.W.: Anaesthetize those planaria, Turtox News 35:135, 1957. h. Rose, S.M., University of Illinois, Urbana, Ill.
i. Schatzmann, J.H., Harvard Medical School, Boston, Mass.
j. Taylor, A.C., Rockefeller Institute of Medical Research, New York, N.Y. k. Thornton, C.S., Kenyon College, Dept. of Biology, Gambier, Ohio.
l. Van Stone, J.M., Trinity College, Dept. of Biology, Hartford, Conn, Cited in Bove, FJ., MS-222 Sandoz-the anesthetic of choice for fish and other cold-blooded organisms,
Sandoz News, no.3, 12p., 1962.
4. Schoettger, R.A., and Julin, A.M.: Investigations in Fish Control: 13. Efficacy of MS-222 as an Anesthetic on Four Salmonids, U.S. Bureau of Sport Fisheries and Wildlife,
Resource Publication 19, 1966.
5. Schoettger, R.A.: Efficacy of MS-222 as an Anesthetic for Northern Pike, Muskellunge and Walleye, U.S. Bureau of Sport Fisheries and Wildlife.
6. Knight, A.E.: Intracellular hemoglobin crystallization in two centrarchids, the large-mouth bass and the bluegill, Progressive Fish Culturist 26:115 (no. 3) 1964.
7. Lumb, W.V. Anesthesia of Laboratory and Zoo Animals, in: Small Animal Anesthesia, Philadelphia, Lea and Febiger, 1963, pp. 269-310.
8. Webb, R.T., Distribution of bluegill treated with tricaine methanesulfonate (MS-222), Progressive Fish-Culturist 20:69 (no. 2) 1958.
9. Klontz, G.W.: Anesthesia of fishes, Proceedings of the Symposium on Experimental
Animal Anesthesiology, Brooks Air Force Base, Dec. 14-16, 13p., 1964.
10. Gilbert, P.W., and Wood, F. G.: Methods of anesthetizing large sharks and rays safely

Salamander Concentration* Duration of
Anesthesia*

and rapidly. Science 126: 212, 1957.
11. Mann, H., and Rajbanshi, K.G.: Anesthetic and Tranquilizer for Fish, Frogs and other

Cold-blooded Organisms, Sandoz Bulletin No. 3350/182 e. Basle, Switzerland.

12. Tuumanen, P.: Experiments with MS-222 Sandoz in the Shipment of Live Trout in
Plastic Pouches, Kalataloudellisen tukimostoimiston, Tiedomantoja, no. 2, 1966.
13. Lemarque, P.: Anesthesie et transport, Bull, Inf. Cons. Sup. Pêche 55:5, 1964.
14. Walker, C.R., and Schoettger, R.A.: Investigations in Fish Control: 15. Residues of MS-
222 in Four Salmonids Following Anesthesia, U.S. Bureau of Sport Fisheries and Wildlife, Resource Publication 21, 1966.
15. Correspondence: Bureau of Fisheries, U.S. Department of Interior, 1968.

Manufactured by:
Syndel
1441 W. Smith Road Ferndale, WA 98248

FAX (360) 384-0270
www.syndel.com
ver. 010322

Approved by FDA under ANADA # 200-226